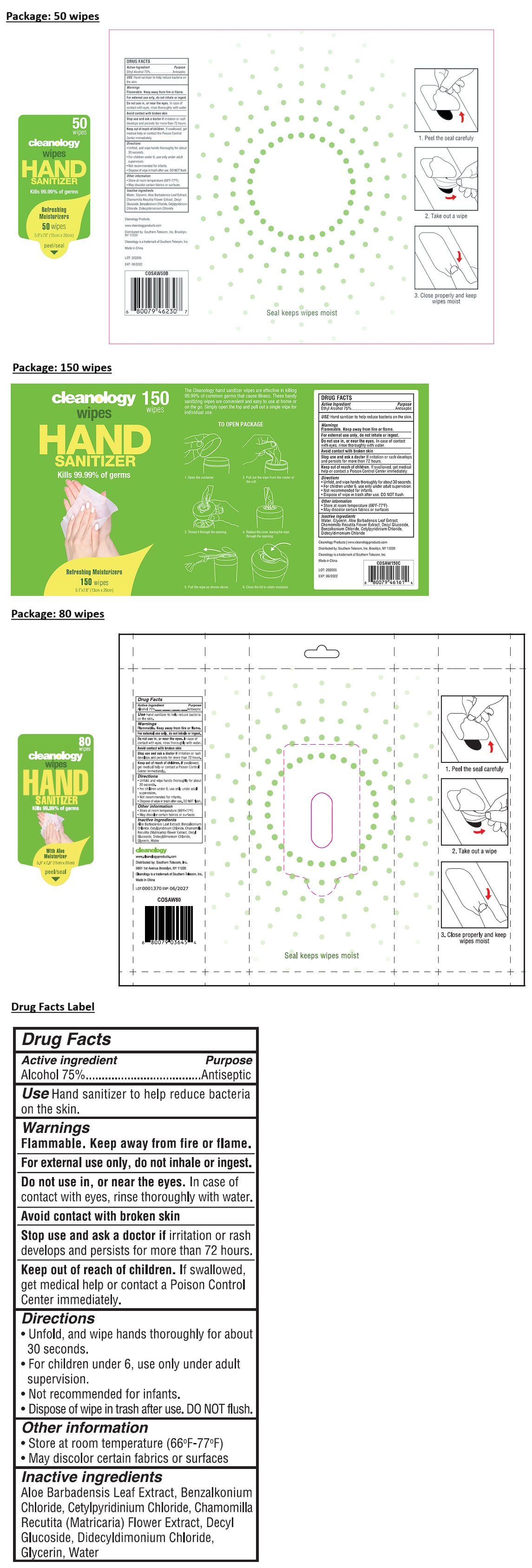 DRUG LABEL: Hand Sanitizer Wipes
NDC: 76546-002 | Form: CLOTH
Manufacturer: Southern Telecom, Inc.
Category: otc | Type: HUMAN OTC DRUG LABEL
Date: 20250605

ACTIVE INGREDIENTS: ALCOHOL 0.75 mL/1 1
INACTIVE INGREDIENTS: ALOE VERA LEAF; BENZALKONIUM CHLORIDE; CETYLPYRIDINIUM CHLORIDE; CHAMOMILE; DECYL GLUCOSIDE; DIDECYLDIMONIUM CHLORIDE; GLYCERIN; WATER

cleanology wipes

Active ingredient

Alcohol 75%

Purpose

Antiseptic

Use

Hand sanitizer to help reduce bacteria on the skin.

Warnings

Flammable. Keep away from fire or flame.

For external use only, do not inhale or ingest.

Do not use in, or near eyes. In case of contact with eyes, rinse thoroughly with water.

Avoid contact with broken skin

Stop use and ask a doctor if irritation or rash develops and persists for more than 72 hours.

Keep out of reach of children. If swallowed, get medical help or contact a Poison Control Center immediately.

Directions

• Unfold, and wipe hands thoroughly for about 30 seconds.
• For children under 6, use only under adult supervision.
• Not recommended for infants.
• Dispose of wipe in trash after use. DO NOT flush.

Other information

• Store at room temperature (66°F-77°F)
• May discolor certain fabrics or surfaces

Inactive ingredients

Aloe Barbadensis Leaf Extract, Benzalkonium Chloride, Cetylpyridinium Chloride, Chamomilla Recutita (Matricaria) Flower Extract, Decyl Glucoside, Didecyldimonium Chloride, Glycerin, Water

Kills 99.99% of germs

With Aloe Moisturizer

Seal keeps wipes moist

1. Peel the seal carefully

2. Take out a wipe

3. Close properly and keep wipes moist

Cleanology

www.cleanologyproducts.com

Distributed by: Southern Telecom, Inc.

5601 1st Avenue Brooklyn, NY 11220

Cleanology is a trademark of Southern Telecom, Inc.

Made in China